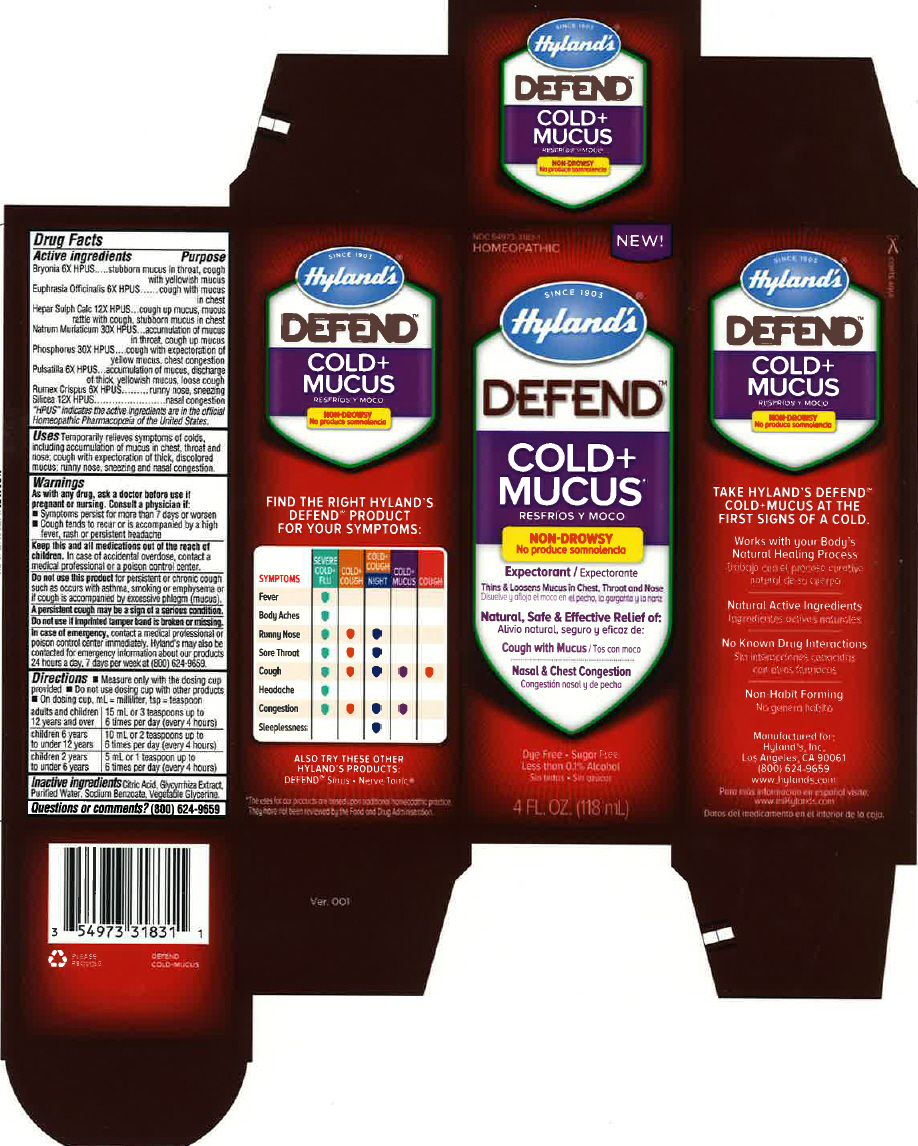 DRUG LABEL: Defend Cold and Mucus
NDC: 54973-3183 | Form: LIQUID
Manufacturer: Hyland's Inc.
Category: homeopathic | Type: HUMAN OTC DRUG LABEL
Date: 20221212

ACTIVE INGREDIENTS: BRYONIA ALBA ROOT 6 [hp_X]/1 mL; EUPHRASIA STRICTA 6 [hp_X]/1 mL; CALCIUM SULFIDE 12 [hp_X]/1 mL; SODIUM CHLORIDE 30 [hp_X]/1 mL; PHOSPHORUS 30 [hp_X]/1 mL; PULSATILLA PATENS WHOLE 6 [hp_X]/1 mL; RUMEX CRISPUS ROOT 6 [hp_X]/1 mL; SILICON DIOXIDE 12 [hp_X]/1 mL
INACTIVE INGREDIENTS: CITRIC ACID MONOHYDRATE; GLYCYRRHIZA GLABRA; WATER; SODIUM BENZOATE; GLYCERIN

Defend Cold and Mucus

Drug Facts

ACTIVE INGREDIENT

Active Ingredients | Purpose
Bryonia 6X HPUS | stubborn mucus in throat, cough with yellowish mucus
Euphrasia Officinalis 6X HPUS | cough with mucus in chest
Hepar Sulph Calc 12X HPUS | cough up mucus, mucus rattle with cough, stubborn mucus in chest
Natrum Muriaticum 30X HPUS | accumulation of mucus in throat, cough up mucus
Phosphorus 30X HPUS | cough with expectoration of yellow mucus, chest congestion
Pulsatilla 6X HPUS | accumulation of mucus, discharge of thick, yellowish mucus, loose cough
Rumex Crispus 6X HPUS | runny nose, sneezing
Silicea 12X HPUS | nasal congestion
"HPUS" indicates the active ingredients are in the official Homeopathic Pharmacopœia of the United States.

Uses

Temporarily relieves symptoms of colds, including accumulation of mucus in chest, throat and nose; cough with expectoration of thick, discolored mucus; runny nose, sneezing and nasal congestion.

Warnings

PREGNANCY OR BREAST FEEDING

As with any drug, ask a doctor before use if pregnant or nursing. Consult a physician if:

- Symptoms persist for more than 7 days or worsen
- Cough tends to recur or is accompanied by a high fever, rash or persistent headache

KEEP OUT OF REACH OF CHILDREN

Keep this and all medications out of the reach of children. In case of accidental overdose, contact a medical professional or a poison control center.

Do not use this product for persistent or chronic cough such as occurs with asthma, smoking or emphysema or if cough is accompanied by excessive phlegm (mucus).

A persistent cough may be a sign of a serious condition.

Do not use if imprinted tamper band is broken or missing.

In case of emergency, contact a medical professional or poison control center immediately. Hyland's may also be contacted for emergency information about our products 24 hours a day, 7 days per week at (800) 624-9659.

Directions

- Measure only with the dosing cup provided
- Do not use dosing cup with other products
- On dosing cup, mL = millimeter, tsp = teaspoon

adults and children 12 years and over | 15 mL or 3 teaspoons up to 6 times per day (every 4 hours)
children 6 years to under 12 years | 10 mL or 2 teaspoons up to 6 times per day (every 4 hours)
children 2 years to under 6 years | 5 mL or 1 teaspoon up to 6 times per day (every 4 hours)

Inactive Ingredients

Citric Acid, Glycyrrhiza Extract, Purified Water, Sodium Benzoate, Vegetable Glycerine.

Questions or comments?

(800) 624-9659

PRINCIPAL DISPLAY PANEL - 118 mL Bottle Carton

NDC 54973-3183-1
HOMEOPATHIC

NEW!

SINCE 1903
Hyland's®

DEFEND™

COLD+
MUCUS*

NON-DROWSY

Expectorant

Thins & Loosens Mucus in Chest, Throat and Nose

Natural, Safe & Effective Relief of:

Cough with Mucus

Nasal & Chest Congestion

Dye Free • Sugar Free
Less than 0.1% Alcohol

4 FL. OZ. (118 mL)